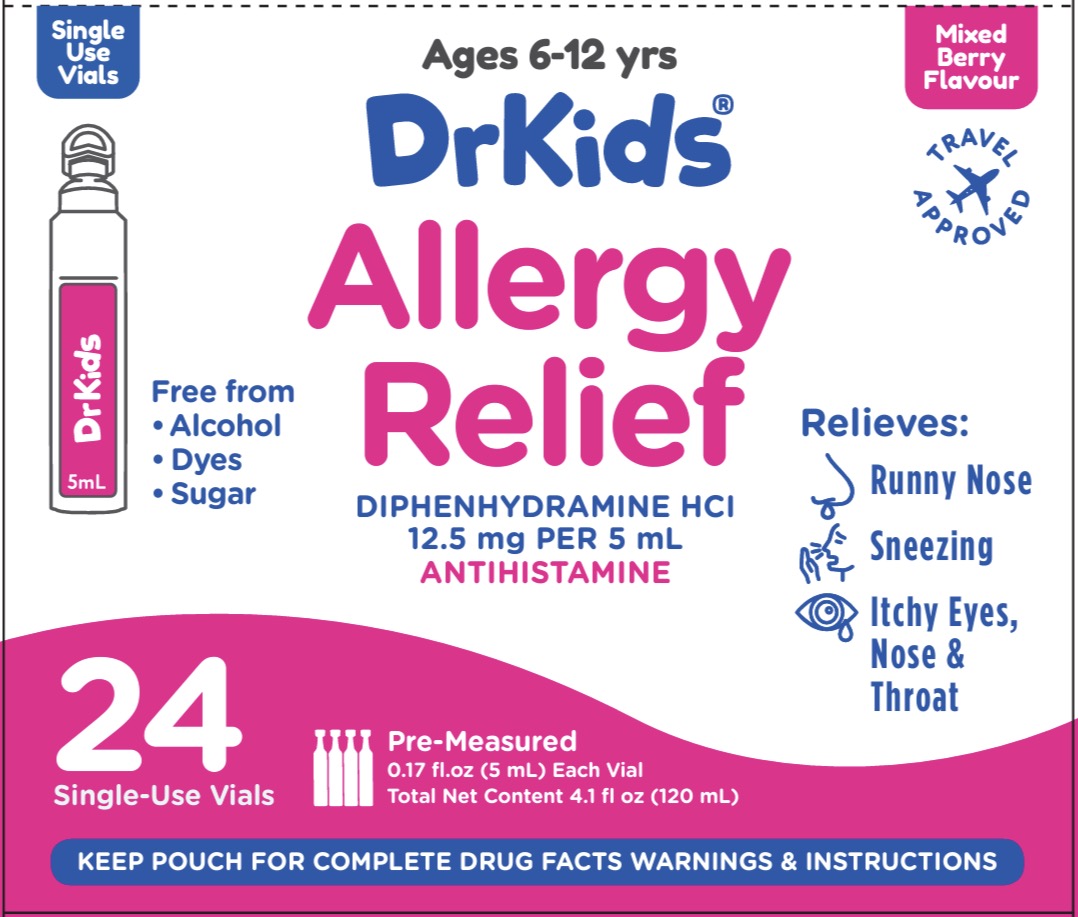 DRUG LABEL: Dr Kids
NDC: 73282-2521 | Form: SOLUTION
Manufacturer: CalmCo LLC
Category: otc | Type: HUMAN OTC DRUG LABEL
Date: 20250926

ACTIVE INGREDIENTS: DIPHENHYDRAMINE HYDROCHLORIDE 12.5 mg/5 mL
INACTIVE INGREDIENTS: SUCRALOSE; ANHYDROUS CITRIC ACID; SORBITOL; SODIUM BENZOATE; GLYCERIN; WATER; PROPYLENE GLYCOL; XYLITOL; CARBOXYMETHYLCELLULOSE

DrKids Children's Allergy Relief (LA)

Active Ingredient and Purpose

Active ingredient (in each 5 mL vial) | Purpose
Diphenhydramine HCl 12.5 mg............... | Antihistamine

Uses

Temporarily relieves

- runny nose
- sneezing
- itchy, watery eyes due to hay fever
- itchy nose or throat
- other upper respiratory allergies

Warnings

.

Do not use

- with any other product containing diphenhydramine, even one used on skin

Ask a doctor before use if your child has

- glaucoma
- a breathing problem such as chronic bronchitis

Ask a doctor or pharmacist before use if your child is

taking sedatives or tranquilizers

When using this product

- may cause excitability in children
- may cause marked drowsiness
- sedatives and tranquilizers may increase the drowsiness effect

KEEP OUT OF REACH OF CHILDREN.

In case of accidental overdose, get medical help or contact a Poison Control Center right away (1-800-222-1222).

Directions

- do not exceed 12 vials in a 24-hour period
- follow the “Easy to Use” instructions on pouch

Age | Dose
children 6 to 12 years | 1 - 2 vials every 4-6 hours
children under 6 years | consult a doctor

Other information

- each 5 mL vial contains: sodium 2 mg
- store between 68-77°F (20-25°C)
- do not use if pouch has been torn open or vial is punctured or open

Inactive ingredients

anhydrous citric acid, carboxymethylcellulose, flavors, glycerin, propylene glycol, sodium benzoate, sorbitol, sucralose, xylitol, water

Questions or comments?

(M-F) 9AM-5PM EST or visit www.DrKids.com

Distributed by: CalmCo LLC, Sarasota, FL 34240